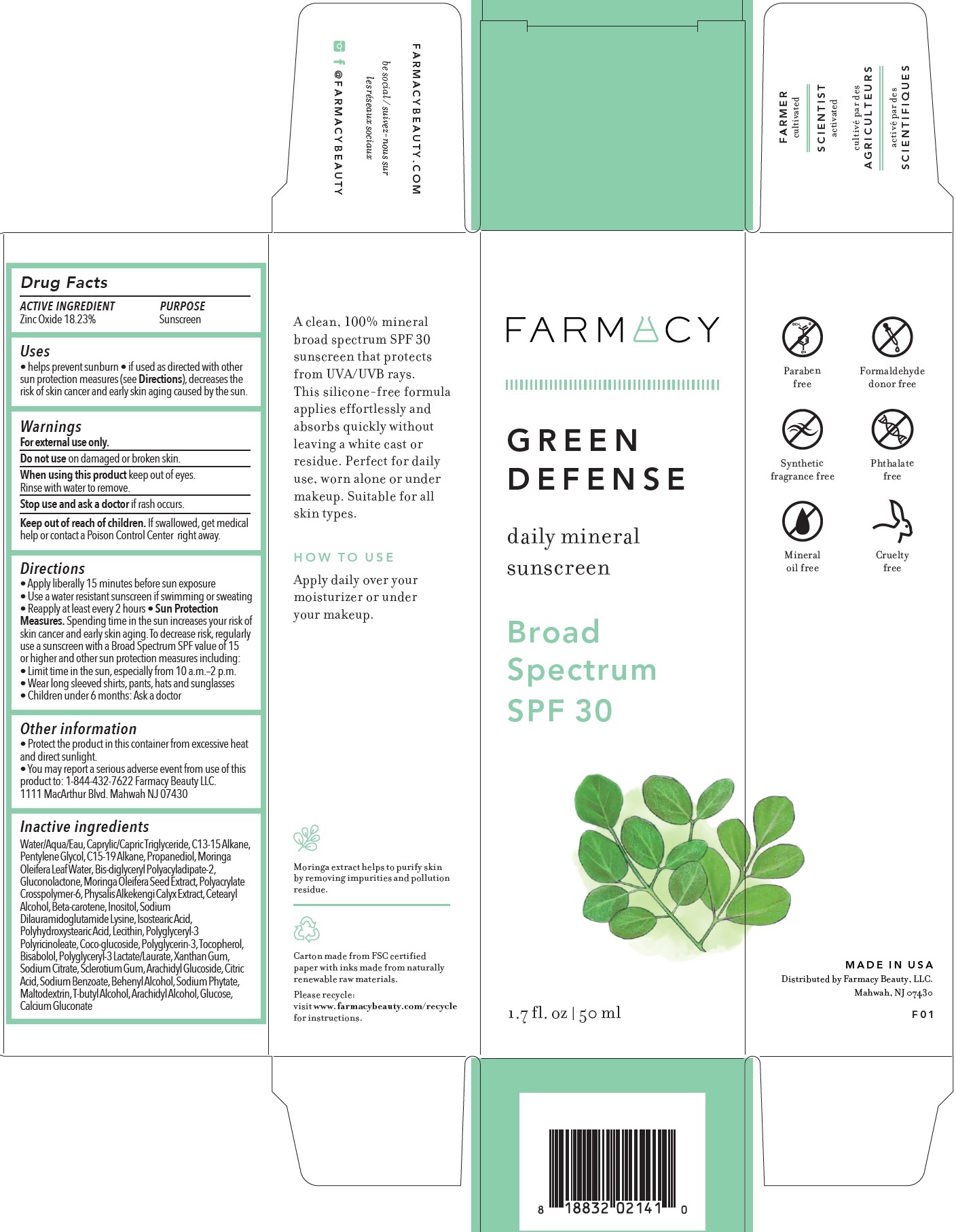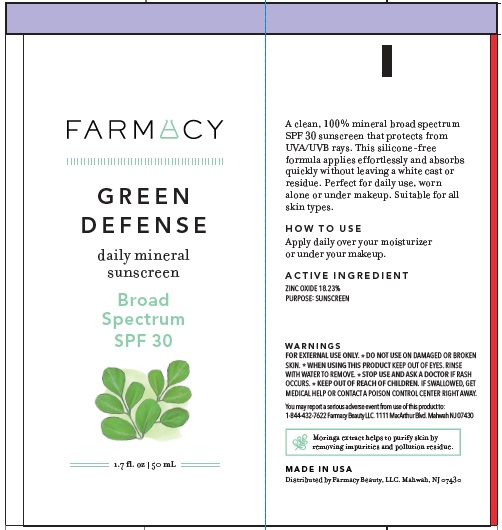 DRUG LABEL: Green Defense daily mineral sunscreen Broad Spectrum SPF 30
NDC: 72830-265 | Form: LOTION
Manufacturer: Farmacy Beauty LLC
Category: otc | Type: HUMAN OTC DRUG LABEL
Date: 20231028

ACTIVE INGREDIENTS: ZINC OXIDE 182.3 mg/1 mL
INACTIVE INGREDIENTS: WATER; MEDIUM-CHAIN TRIGLYCERIDES; C13-15 ALKANE; PENTYLENE GLYCOL; C15-19 ALKANE; PROPANEDIOL; MORINGA OLEIFERA LEAF; BIS-DIGLYCERYL POLYACYLADIPATE-2; GLUCONOLACTONE; AMMONIUM ACRYLOYLDIMETHYLTAURATE, DIMETHYLACRYLAMIDE, LAURYL METHACRYLATE AND LAURETH-4 METHACRYLATE COPOLYMER, TRIMETHYLOLPROPANE TRIACRYLATE CROSSLINKED (45000 MPA.S); PHYSALIS ALKEKENGI CALYX; CETOSTEARYL ALCOHOL; BETA CAROTENE; INOSITOL; SODIUM DILAURAMIDOGLUTAMIDE LYSINE; ISOSTEARIC ACID; POLYGLYCERYL-3 PENTARICINOLEATE; COCO GLUCOSIDE; POLYGLYCERIN-3; TOCOPHEROL; LEVOMENOL; XANTHAN GUM; SODIUM CITRATE; BETASIZOFIRAN; ARACHIDYL GLUCOSIDE; CITRIC ACID MONOHYDRATE; SODIUM BENZOATE; DOCOSANOL; PHYTATE SODIUM; MALTODEXTRIN; TERT-BUTYL ALCOHOL; ARACHIDYL ALCOHOL; ANHYDROUS DEXTROSE; CALCIUM GLUCONATE

Green Defense daily mineral sunscreen Broad Spectrum SPF 30

ACTIVE INGREDIENT

Zinc Oxide 18.23%

PURPOSE

Sunscreen

Uses

• helps prevent sunburn • if used as directed with other sun protection measures (see), decreases the risk of skin cancer and early skin aging caused by the sun. Directions

Warnings

For external use only.

Do not use

on damaged or broken skin.

When using this product

keep out of eyes. Rinse with water to remove.

Stop use and ask a doctor

if rash occurs.

Keep out of reach of children.

If swallowed, get medical help or contact a Poison Control Center right away.

Directions

• Apply liberally 15 minutes before sun exposure • Use a water resistant sunscreen if swimming or sweating • Reapply at least every 2 hours

• Spending time in the sun increases your risk of skin cancer and early skin aging. To decrease risk, regularly use a sunscreen with a Broad Spectrum SPF value of 15 or higher and other sun protection measures including: • Limit time in the sun, especially from 10 a.m.–2 p.m. • Wear long sleeved shirts, pants, hats and sunglasses • Children under 6 months: Ask a doctor Sun Protection Measures.

Other information

• Protect the product in this container from excessive heat and direct sunlight. • You may report a serious adverse event from use of this product to: 1-844-432-7622 Farmacy Beauty LLC. 1111 MacArthur Blvd. Mahwah NJ 07430

Inactive ingredients

Water/Aqua/Eau, Caprylic/Capric Triglyceride, C13-15 Alkane, Pentylene Glycol, C15-19 Alkane, Propanediol, Moringa Oleifera Leaf Water, Bis-diglyceryl Polyacyladipate-2, Gluconolactone, Moringa Oleifera Seed Extract, Polyacrylate Crosspolymer-6, Physalis Alkekengi Calyx Extract, Cetearyl Alcohol, Beta-carotene, Inositol, Sodium Dilauramidoglutamide Lysine, Isostearic Acid, Polyhydroxystearic Acid, Lecithin, Polyglyceryl-3 Polyricinoleate, Coco-glucoside, Polyglycerin-3, Tocopherol, Bisabolol, Polyglyceryl-3 Lactate/Laurate, Xanthan Gum, Sodium Citrate, Sclerotium Gum, Arachidyl Glucoside, Citric Acid, Sodium Benzoate, Behenyl Alcohol, Sodium Phytate, Maltodextrin, T-butyl Alcohol, Arachidyl Alcohol, Glucose, Calcium Gluconate